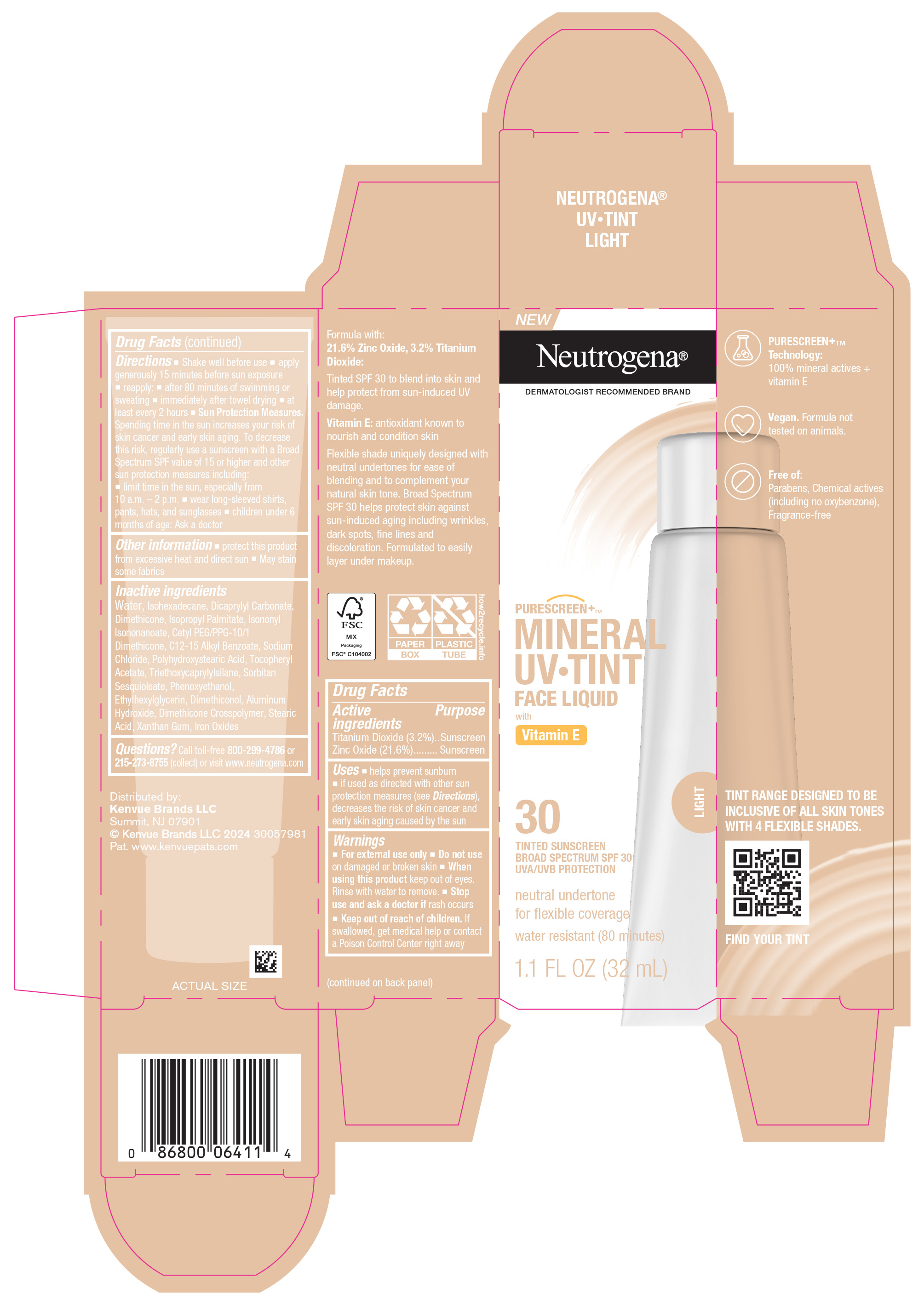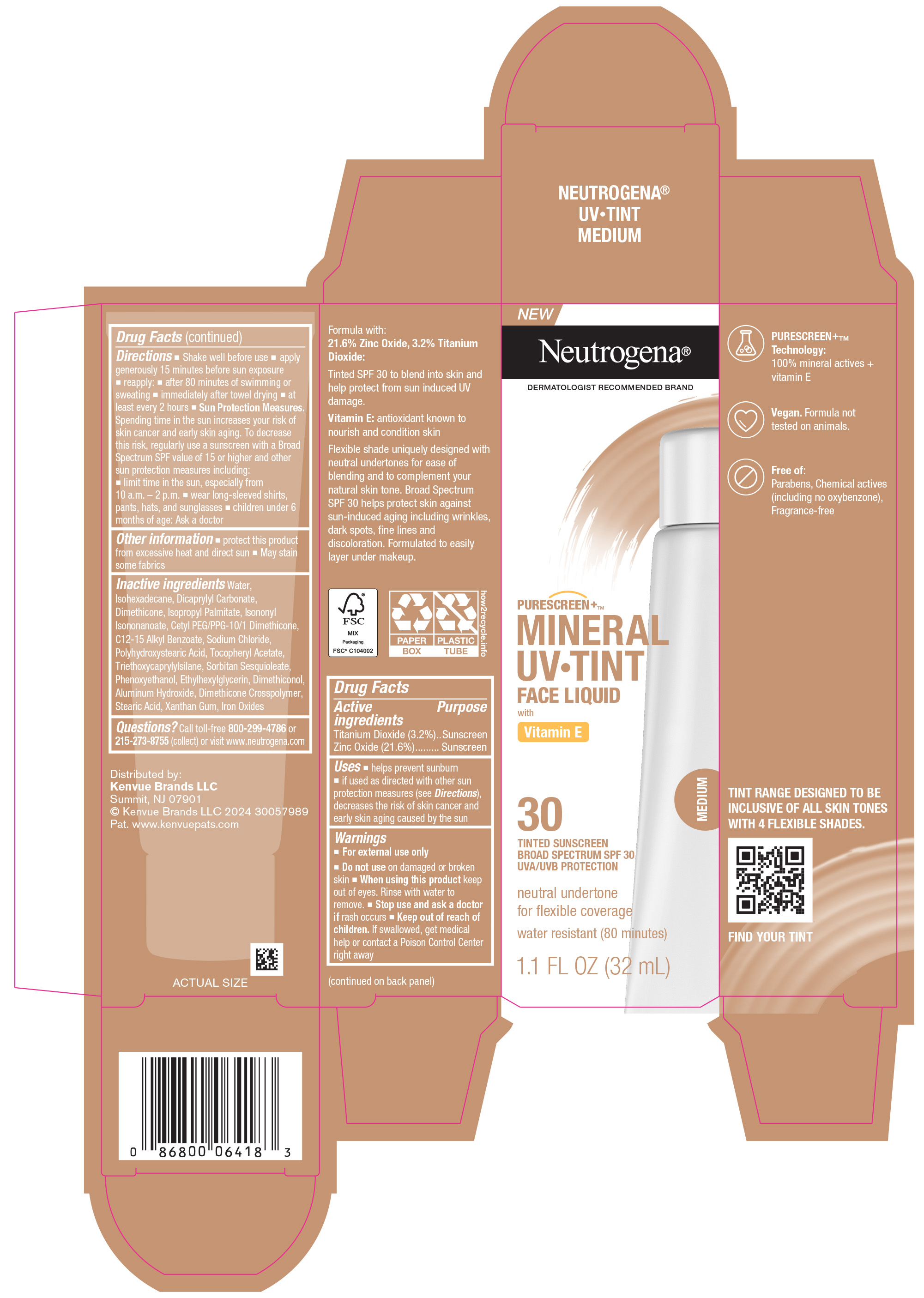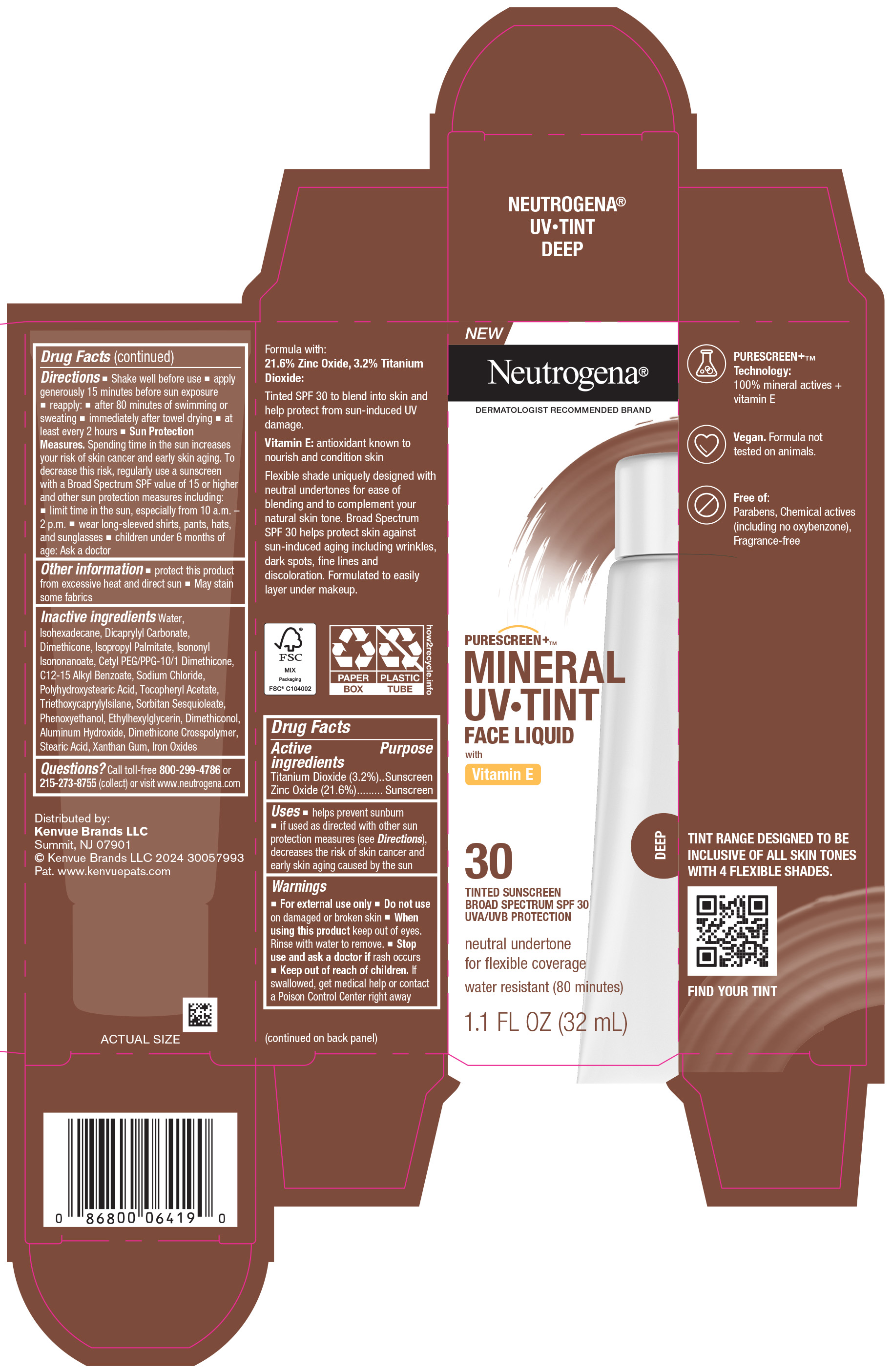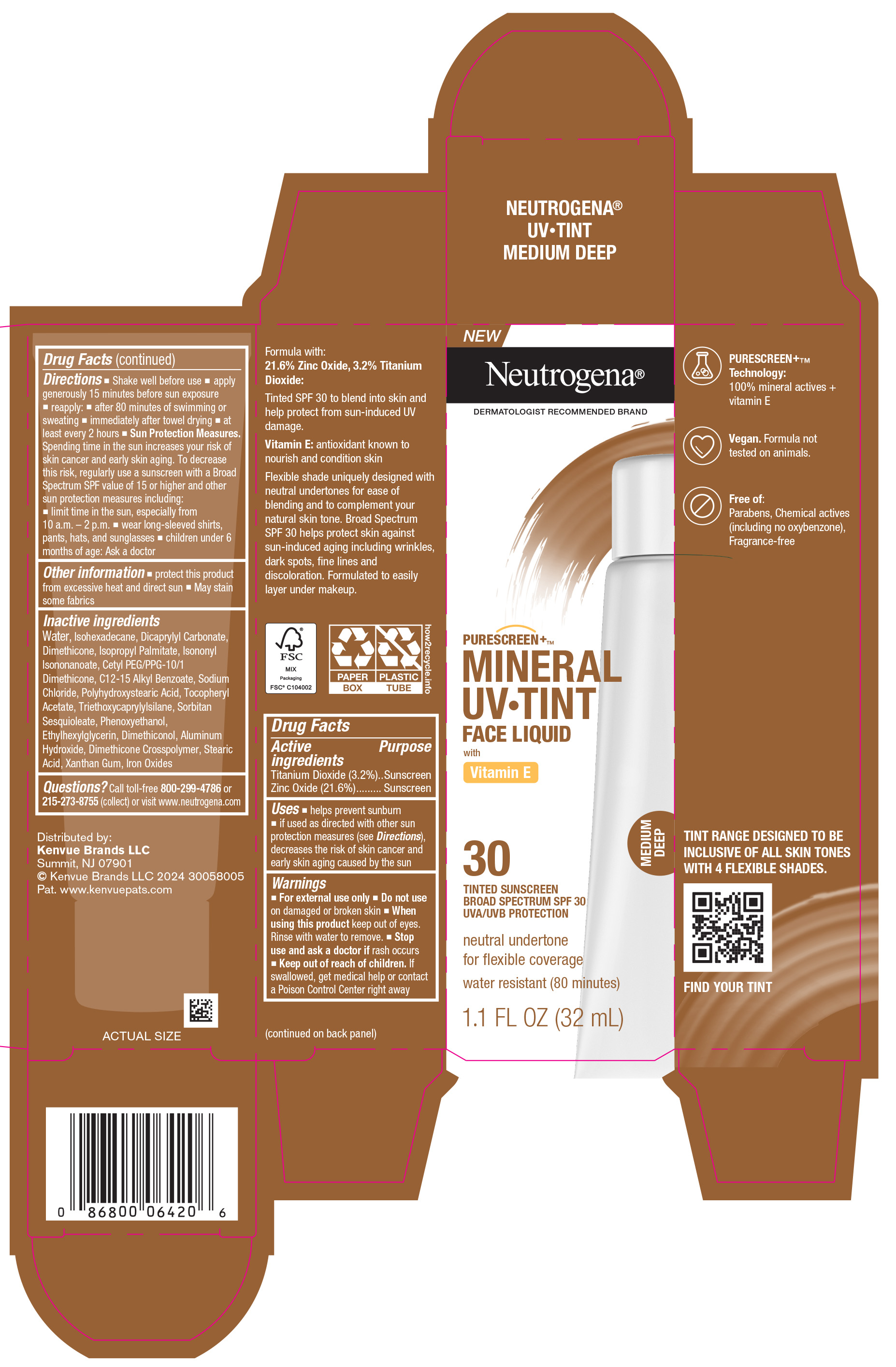 DRUG LABEL: Neutrogena MINERAL UV TINT FACE MEDIUM DEEP SPF 30
NDC: 69968-0784 | Form: LOTION
Manufacturer: Kenvue Brands LLC
Category: otc | Type: HUMAN OTC DRUG LABEL
Date: 20241113

ACTIVE INGREDIENTS: ZINC OXIDE 216 mg/1 mL; TITANIUM DIOXIDE 32 mg/1 mL
INACTIVE INGREDIENTS: WATER; ISOHEXADECANE; DIMETHICONE; ISOPROPYL PALMITATE; CETYL PEG/PPG-10/1 DIMETHICONE (HLB 5); ALKYL (C12-15) BENZOATE; SODIUM CHLORIDE; PHENOXYETHANOL; ETHYLHEXYLGLYCERIN; ALUMINUM HYDROXIDE; XANTHAN GUM; FERRIC OXIDE RED; STEARIC ACID; TRIETHOXYCAPRYLYLSILANE; .ALPHA.-TOCOPHEROL ACETATE; DICAPRYLYL CARBONATE; ISONONYL ISONONANOATE; SORBITAN SESQUIOLEATE; DIMETHICONE CROSSPOLYMER (450000 MPA.S AT 12% IN CYCLOPENTASILOXANE)

Neutrogena MINERAL UV TINT FACE LIQUID SPF 30

Drug Facts

Active ingredients

Titanium Dioxide 3.2%, Zinc Oxide 21.6%

Purpose

Sunscreen

Uses

- helps prevent sunburn
- if used as directed with other sun protection measures (see Directions), decreases the risk of skin cancer and early skin aging caused by the sun

Warnings

For external use only

- Do not use on damaged or broken skin

- When using this product keep out of eyes . Rinse with water to remove.

- Stop use and ask a doctor if rash occurs

- Keep out of reach of children. If swallowed, get medical help or contact a Poison Control Center right away.

Directions

- Shake well before use
- apply generously 15 minutes before sun exposure
- reapply:
- after 80 minutes of swimming or sweating
- immediately after towel drying
- at least every 2 hours
- Sun Protection Measures: Spending time in the sun increases your risk of skin cancer and early skin aging . To decrease this risk, regularly use a sunscreen with a Broad Spectrum SPF value of 15 or higher and other sun protection measures including:
  - limit time in the sun, especially from 10 a.m. - 2 p.m.
  - wear long-sleeved shirts, pants, hats, and sunglasses
- children under 6 months of age: Ask a doctor

Other information

- protect this product from excessive heat and direct sun
- May stain some fabrics

Inactive ingredients

Water, Isohexadecane, Dicaprylyl Carbonate, Dimethicone, Isopropyl Palmitate, Isononyl Isononanoate, Cetyl PEG/PPG-10/1 Dimethicone, C12-15 Alkyl Benzoate, Sodium Chloride, Polyhydroxystearic Acid, Tocopheryl Acetate, Triethoxycaprylylsilane, Sorbitan Sesquioleate, Phenoxyethanol, Ethylhexylglycerin, Dimethiconol, Aluminum Hydroxide, Dimethicone Crosspolymer, Stearic Acid, Xanthan Gum, Iron Oxides

Questions?

Call toll-free 800-299-4786 or 215-273-8755 (collect) or visit www.neutrogena.com

Distributed by:
Kenvue Brands LLC

Summit, NJ 07901

PRINCIPAL DISPLAY PANEL - 32 mL Carton Label - LIGHT

NEW

Neutrogena®

DERMATOLOGIST RECOMMENDED BRAND

PURESCREEN+ TM

MINERAL

UV ● TINT

FACE LIQUID

with

Vitamin E

LIGHT

30

TINTED SUNSCREEN

BROAD SPECTRUM SPF 30

UVA/UVB PROTECTION

neutral undertone

for flexible coverage

water resistant (80 minutes)

1.1 FL OZ (32mL)

PRINCIPAL DISPLAY PANEL - 32 mL Carton Label - DEEP

NEW

Neutrogena®

DERMATOLOGIST RECOMMENDED BRAND

PURESCREEN+ TM

MINERAL

UV ● TINT

FACE LIQUID

with

Vitamin E

DEEP

30

TINTED SUNSCREEN

BROAD SPECTRUM SPF 30

UVA/UVB PROTECTION

neutral undertone

for flexible coverage

water resistant (80 minutes)

1.1 FL OZ (32mL)

PRINCIPAL DISPLAY PANEL - 32 mL Carton Label - MEDIUM

NEW

Neutrogena®

DERMATOLOGIST RECOMMENDED BRAND

PURESCREEN+ TM

MINERAL

UV ● TINT

FACE LIQUID

with

Vitamin E

MEDIUM

30

TINTED SUNSCREEN

BROAD SPECTRUM SPF 30

UVA/UVB PROTECTION

neutral undertone

for flexible coverage

water resistant (80 minutes)

1.1 FL OZ (32mL)

PRINCIPAL DISPLAY PANEL - 32 mL Carton Label - MEDIUM DEEP

NEW

Neutrogena®

DERMATOLOGIST RECOMMENDED BRAND

PURESCREEN+ TM

MINERAL

UV ● TINT

FACE LIQUID

with

Vitamin E

MEDIUM

DEEP

30

TINTED SUNSCREEN

BROAD SPECTRUM SPF 30

UVA/UVB PROTECTION

neutral undertone

for flexible coverage

water resistant (80 minutes)

1.1 FL OZ (32mL)